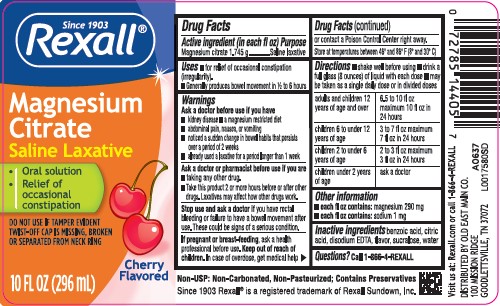 DRUG LABEL: citroma
NDC: 55910-961 | Form: LIQUID
Manufacturer: Old East Main Co.
Category: otc | Type: HUMAN OTC DRUG LABEL
Date: 20260302

ACTIVE INGREDIENTS: MAGNESIUM CITRATE 1.745 g/29.6 mL
INACTIVE INGREDIENTS: BENZOIC ACID; CITRIC ACID MONOHYDRATE; EDETATE DISODIUM ANHYDROUS; SUCRALOSE; WATER

Rexall 164.000/164AA Rev 2 - AB
Cherry Magnesium Citrate

Active ingredient (in each fl oz)

Magnesium citrate 1.745 g

Purpose

Saline laxative

Uses

- for relief of occasional constipation (irregularity).
- Generally produces bowel movement in 1/2 to 6 hours

Warnings

for this product

Ask a doctor before use if you have

- kidney disease
- a magnesium restricted diet
- abdominal pain, nausea, or vomiting
- noticed a sudden change in bowel habits that persists over a period of 2 weeks
- already used a laxative for a period longer than 1 week

Ask a doctor or pharmacist before use if you are

- taking any other drug.
- Take this product 2 or more hours before or after other drugs. Laxatives may affect how other drugs work.

Stop use and ask a doctor if

you have rectal bleeding or failure to have a bowel movement after use. These could be signs of a serious condition.

if pregnant or breast-feeding,

ask help professional before use.

Keep out of reach of children.

In case of overdose, get medical help or contact a Poison Control Center right away.

Storage

Store at temperatures betweem 46° and 86°F (8° and 30° C)

Directions

- shake well before using
- drink a full glass (8 ounces) of liquid with each dose
- may be taken as a single daily dose or in divided doses

adults and children 12 years of age and over - 6.5 to 10 fl oz maximum 10 fl oz in 24 hours

children 6 to under 12 years of age - 3 to 7 fl oz maximum 7 fl oz in 24 hours

children 2 to under 6 years of age - 2 to 3 fl oz maximum 3 fl oz in 24 hours

children under 2 years of age - ask a doctor

other information

- each fl oz contains: magnesium 290 mg
- each fl oz contains: sodium 1 mg

Inactive ingredients

benzoic acid, citric acid, disodium EDTA, flavor, sucralose, water

Questions?

Call 1-866-4-REXALL

ADVERSE REACTION

Non-USP: Non-Carbonated, Non-Pasteurized; Contains Preservatives

Since 1903 Rexall® is a registered trademark of Rexall Sundown, Inc.

Visit us at: Rexall.com or call 1-866-4-REXALL

DISTRIBUTED BY OLD EAST MAIN CO.

100 MISSION RIDGE

GOODLETTSVILLE, TN 37072

Principal display panel

Since 1903

Rexall®

Magnesium

Citrate

Saline Laxative

- Oral Solution
- Relief of occasion constipation

DO NOT USE IF TAMPER EVIDENT TWIST-OFF CAP IS MISSING, BROKEN OR SEPARATED FROM NECK RING

Cherry Flavored

10 FL OZ (296 mL)